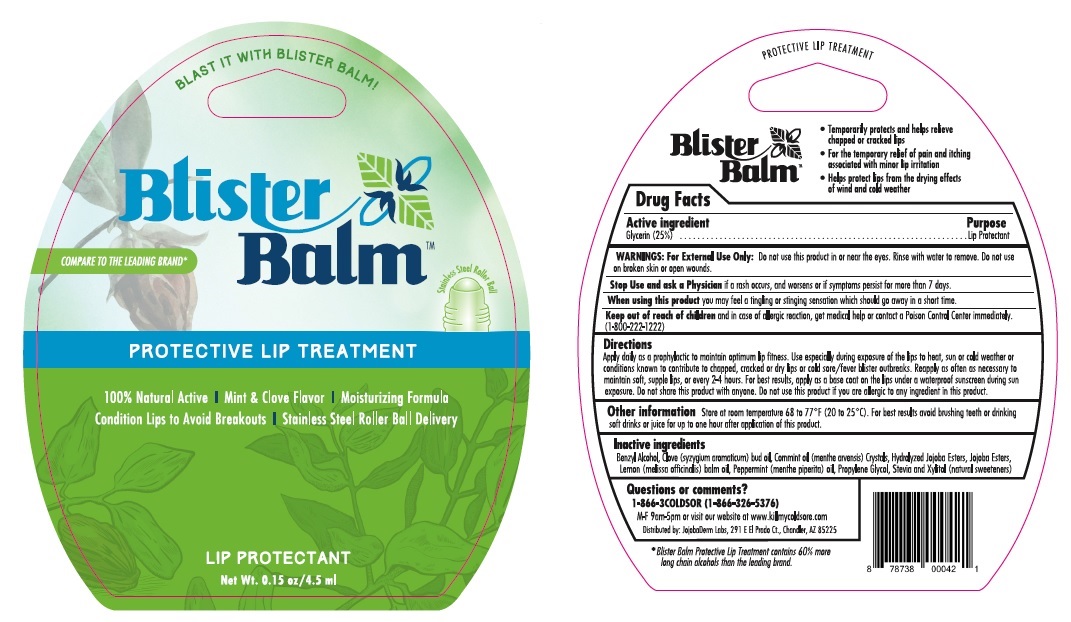 DRUG LABEL: Blister Balm
NDC: 70996-004 | Form: LIQUID
Manufacturer: Floratech Botanicals, LLC
Category: otc | Type: HUMAN OTC DRUG LABEL
Date: 20170217

ACTIVE INGREDIENTS: GLYCERIN 25 g/100 mL
INACTIVE INGREDIENTS: BENZYL ALCOHOL; CLOVE OIL; MENTHA ARVENSIS LEAF OIL; HYDROLYZED JOJOBA ESTERS (ACID FORM); HYDROGENATED JOJOBA OIL, RANDOMIZED; MELISSA OFFICINALIS SEED OIL; PEPPERMINT OIL; PROPYLENE GLYCOL; STEVIA REBAUDIUNA LEAF; XYLITOL

Blister Balm Protective Lip Treatment

Active ingredient

Glycerin (25%)

Purpose

Lip Protectant

INDICATIONS AND USAGE

- Temporarily protects and helps relieve chapped or cracked lips
- For the temporary relief of pain and itching associated with minor lip irritation
- Helps protect lips from the drying effects of wind and cold weather

WARNINGS:

For External Use Only: Do not use this product in or near the eyes. Rinse with water to remove. Do not use on broken skin or open wounds.

Stop Use and ask a Physician if a rash occurs, and worsens or if symptoms persist for more than 7 days.

When using this product you may feel a tingling or stinging sensation which should go away in a short time.

Keep out of reach of children and in case of allergic reaction, get medical help or contact a Poison Control Center immediately. (1800-222-1222)

Directions

Apply daily as a prophylactic to maintain optimum lip fitness. Use especially during exposure of the lips to heat, sun or cold weather or conditions known to contribute to chapped, cracked or dry lips or cold sore/fever blister outbreaks. Reapply as often as necessary to maintain soft, supple lips, or every 2-4 hours. For best results, apply as a base coat on the lips under a waterproof sunscreen during sun exposure. Do not share this product with anyone. Do not use this product if you are allergic to any ingredient in this product.

Other information

Store at room temperature 68 to 77°F (20 to 25°C). For best results avoid brushing teeth or drinking soft drinks or juice for up to one hour after application of this product.

Inactive ingredients

Benzyl Alcohol, Clove (syzygium aromaticum) bud oil, Commint oil (menthe arvensis) Crystals, Hydrolyzed Jojoba Esters, Jojobo Esters, Lemon (melissa officinalis) balm oil, Peppermint (menthe piperita) oil, Propylene Glycol, Stevia and Xylitol (natural sweeteners)

Questions or comments?

1-866-3COLDSOR (1-866-326-5376)

M-F 9am-5pm or visit our website at www.killmycoldsore.com

Distributed by: JojobaDerm Labs, 291 E El Prado Ct., Chandler, AZ 85225

BLAST IT WITH BLISTER BALM!

COMPARE TO THE LEADING BRAND*

Stainless Steel Roller Ball

100% Natural Active | Mint & Clove Flavor | Moisturizing Formula

Condition Lips to Avoid Breakouts | Stainless Steel Roller Ball Delivery

LIP PROTECTANT

* Blister Balm Protective Lip Treatment contains 60% more long chain alcohols than the leading brand.